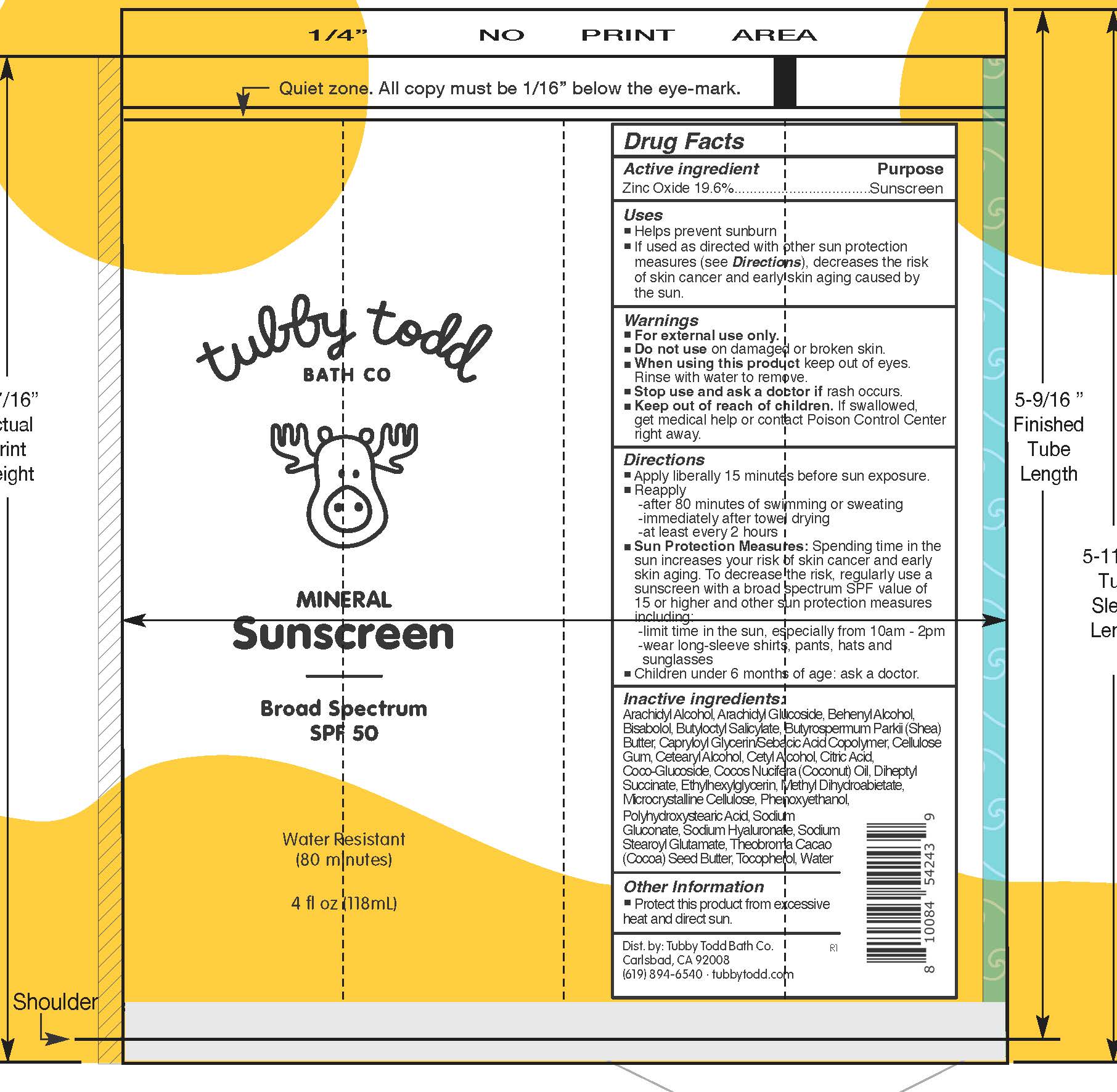 DRUG LABEL: Mineral Sunscreen
NDC: 73088-109 | Form: CREAM
Manufacturer: Tubby Todd
Category: otc | Type: HUMAN OTC DRUG LABEL
Date: 20241222

ACTIVE INGREDIENTS: ZINC OXIDE 19.6 g/100 mL
INACTIVE INGREDIENTS: METHYL DIHYDROABIETATE; THEOBROMA CACAO (COCOA) SEED BUTTER; WATER; CETEARYL ALCOHOL; ARACHIDYL ALCOHOL; BISABOLOL; BUTYLOCTYL SALICYLATE; CAPRYLOYL GLYCERIN/SEBACIC ACID COPOLYMER (2000 MPA.S); CETYL ALCOHOL; CITRIC ACID; COCOS NUCIFERA (COCONUT) OIL; PHENOXYETHANOL; POLYHYDROXYSTEARIC ACID (2300 MW); SODIUM GLUCONATE; SODIUM HYALURONATE; SODIUM STEAROYL GLUTAMATE; ARACHIDYL GLUCOSIDE; ETHYLHEXYLGLYCERIN; BEHENYL ALCOHOL; BUTYROSPERMUM PARKII (SHEA) BUTTER; CELLULOSE GUM; COCO-GLUCOSIDE; DIHEPTYL SUCCINATE; MICROCRYSTALLINE CELLULOSE; TOCOPHEROL

Mineral Sunscreen SPF 50

Active ingredients

Zinc Oxide 19.6%

Purpose

Sunscreen

Uses

• Helps prevent sunburn.
• If used as directed with other sun protection measures (see Directions), decreases the risk of skin cancer and early skin aging caused by the sun.

Warnings

• For external use only.

• Do not use

on damaged or broken skin.

• When using this product

keep out of eyes. Rinse with water to remove.

• Stop use and ask a doctor

if rash occurs.

• Keep out of reach of children.

If swallowed, get medical help or contact a Poison Control Center right away.

Directions

• Apply liberally 15 minutes before sun exposure.
• Reapply
- after 80 minutes of swimming or sweating
- immediately after towel drying
- at least every 2 hours
• Sun Protection Measures: Spending time in the sun increases your risk of skin cancer and early skin aging. To decrease this risk, regularly use a sunscreen with a Broad Spectrum SPF valuor higher and other sun protection measures including:
- limit time in the sun, especially from 10 a.m.-2 p.m.
- wear long-sleeved shirts, pants, hats, and sunglasses
• Children under 6 months of age: ask a doctor

Other information

Protect this product from excessive heat and direct sun.

Inactive ingredients

Arachidyl Alcohol, Arachidyl Glucoside, Behenyl Alcohol, Bisabolol, Butyloctyl Salicylate, Butyrospermum Parkii (Shea) Butter, Capryloyl Glycerin/Sebacic Acid Copolymer, Cellulose Gum, Cetearyl Alcohol, Cetyl Alcohol, Citric Acid, Coco-Glucoside, Cocos Nucifera (Coconut) Oil, Diheptyl Succinate, Ethylhexylglycerin, Methyl Dihydroabietate, Microcrystalline Cellulose, Phenoxyethanol, Polyhydroxystearic Acid, Sodium Gluconate, Sodium Hyaluronate, Sodium Stearoyl Glutamate, Theobroma Cacao (Cocoa) Seed Butter, Tocopherol, Water